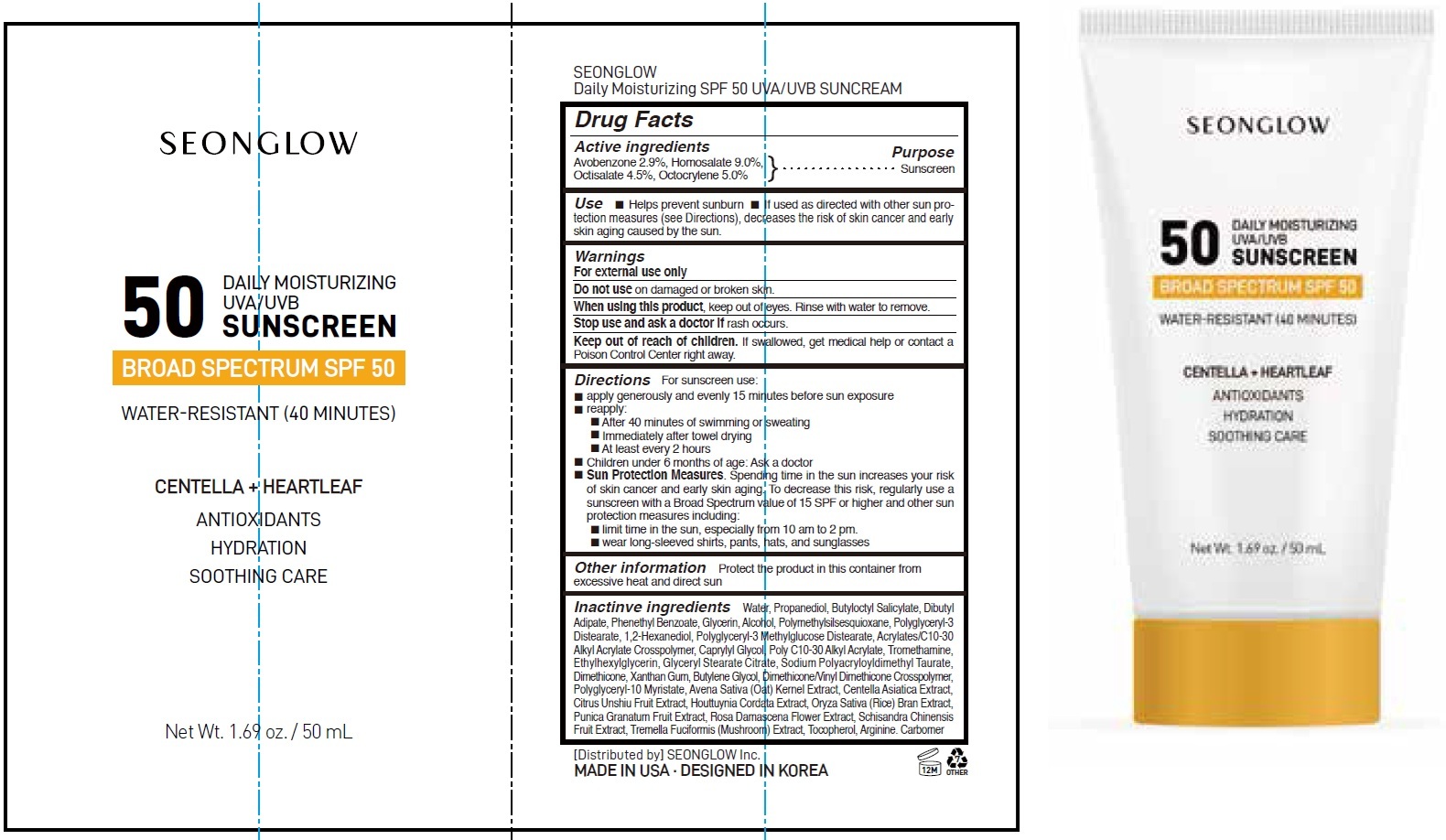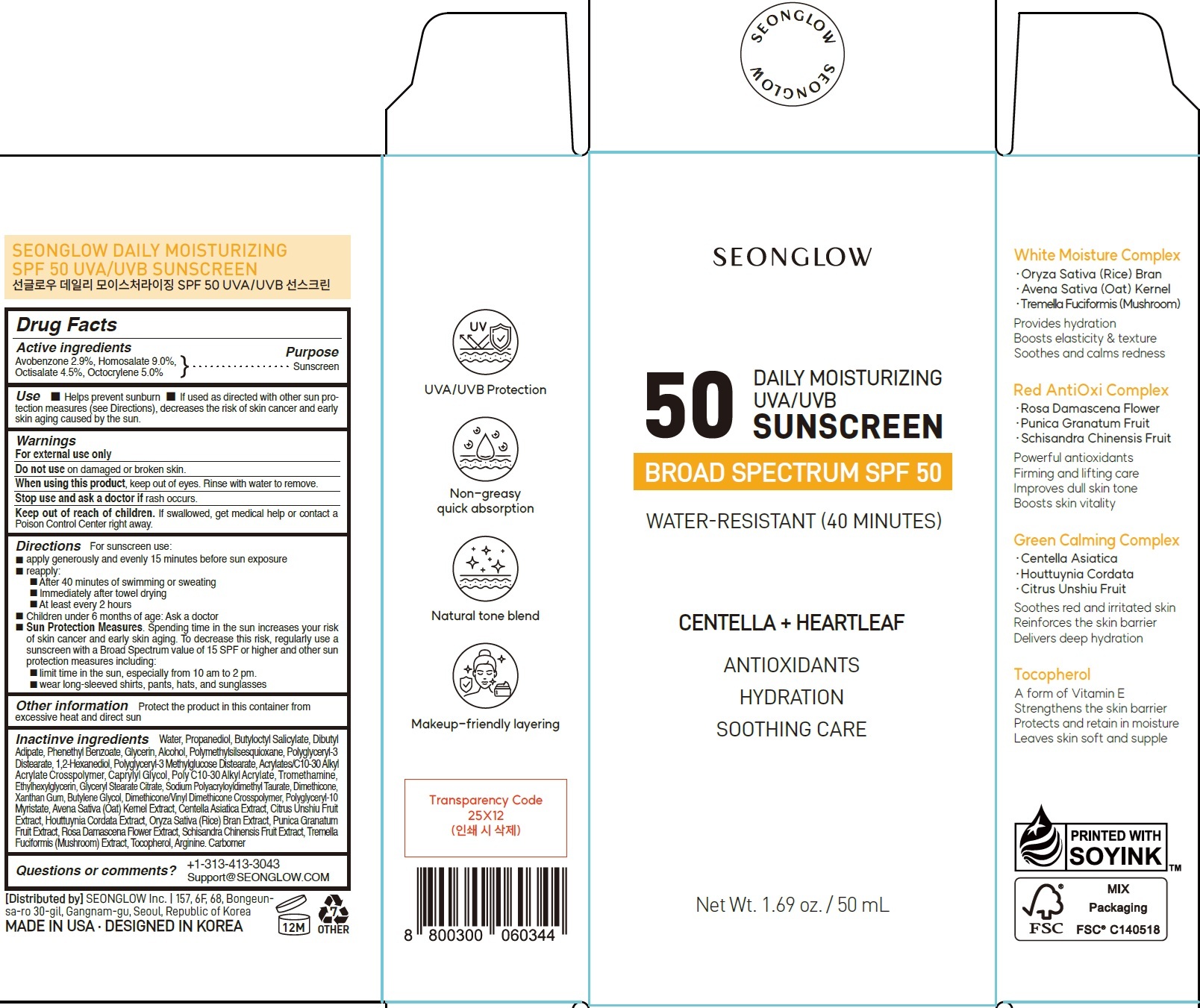 DRUG LABEL: Seonglow Daily Moisturizing Sunscreen SPF 50
NDC: 87249-000 | Form: CREAM
Manufacturer: SeonGlow Inc.
Category: otc | Type: HUMAN OTC DRUG LABEL
Date: 20260226

ACTIVE INGREDIENTS: AVOBENZONE 29 mg/1 mL; HOMOSALATE 90 mg/1 mL; OCTISALATE 45 mg/1 mL; OCTOCRYLENE 50 mg/1 mL
INACTIVE INGREDIENTS: WATER; PROPANEDIOL; BUTYLOCTYL SALICYLATE; DIBUTYL ADIPATE; PHENETHYL BENZOATE; GLYCERIN; ALCOHOL; POLYGLYCERYL-3 DISTEARATE; 1,2-HEXANEDIOL; POLYGLYCERYL-3 METHYLGLUCOSE DISTEARATE; CAPRYLYL GLYCOL; TROMETHAMINE; ETHYLHEXYLGLYCERIN; GLYCERYL STEARATE CITRATE; SODIUM POLYACRYLOYLDIMETHYL TAURATE; DIMETHICONE; XANTHAN GUM; BUTYLENE GLYCOL; POLYGLYCERYL-10 MYRISTATE; OAT; CENTELLA ASIATICA TRITERPENOIDS; TANGERINE; HOUTTUYNIA CORDATA FLOWERING TOP; RICE BRAN; POMEGRANATE; ROSA X DAMASCENA FLOWER; TREMELLA FUCIFORMIS FRUITING BODY; TOCOPHEROL; ARGININE; CARBOMER HOMOPOLYMER, UNSPECIFIED TYPE

Seonglow Daily Moisturizing Sunscreen SPF 50

Active ingredients

Avobenzone 2.9%, Homosalate 9.0%,
Octisalate 4.5%, Octocrylene 5.0%

Purpose

Sunscreen

Use

- Helps prevent sunburn
- If used as directed with other sun protection measures (see Directions), decreases the risk of skin cancer and early skin aging caused by the sun.

Warnings

For external use only

Do not use

on damaged or broken skin.

When using this product,

keep out of eyes. Rinse with water to remove.

Stop use and ask a doctor if

rash occurs.

Keep out of reach of children.

If swallowed, get medical help or contact a Poison Control Center right away.

Directions

For sunscreen use:

- apply generously and evenly 15 minutes before sun exposure
- reapply:
- After 40 minutes of swimming or sweating
- Immediately after towel drying
- At least every 2 hours
- Children under 6 months of age: Ask a doctor
- Sun Protection Measures.Spending time in the sun increases your risk of skin cancer and early skin aging. To decrease this risk, regularly use a sunscreen with a Broad Spectrum value of 15 SPF or higher and other sun protection measures including:
- limit time in the sun, especially from 10 am to 2 pm.
- wear long-sleeved shirts, pants, hats, and sunglasses

Other information

Protect the product in this container from excessive heat and direct sun

Inactive ingredients

Water, Propanediol, Butyloctyl Salicylate, Dibutyl Adipate, Phenethyl Benzoate, Glycerin, Alcohol, Polymethylsilsesquioxane, Polyglyceryl-3 Distearate, 1,2-Hexanediol, Polyglyceryl-3 Methylglucose Distearate, Acrylates/C10-30 Alkyl Acrylate Crosspolymer, Caprylyl Glycol, Poly C10-30 Alkyl Acrylate, Tromethamine, Ethylhexylglycerin, Glyceryl Stearate Citrate, Sodium Polyacryloyldimethyl Taurate, Dimethicone, Xanthan Gum, Butylene Glycol, Dimethicone/Vinyl Dimethicone Crosspolymer, Polyglyceryl-10 Myristate, Avena Sativa (Oat) Kernel Extract, Centella Asiatica Extract, Citrus Unshiu Fruit Extract, Houttuynia Cordata Extract, Oryza Sativa (Rice) Bran Extract, Punica Granatum Fruit Extract, Rosa Damascena Flower Extract, Schisandra Chinensis Fruit Extract, Tremella Fuciformis (Mushroom) Extract, Tocopherol, Arginine. Carbomer

Questions or comments?

+1-313-413-3043 Support@SEONGLOW.COM